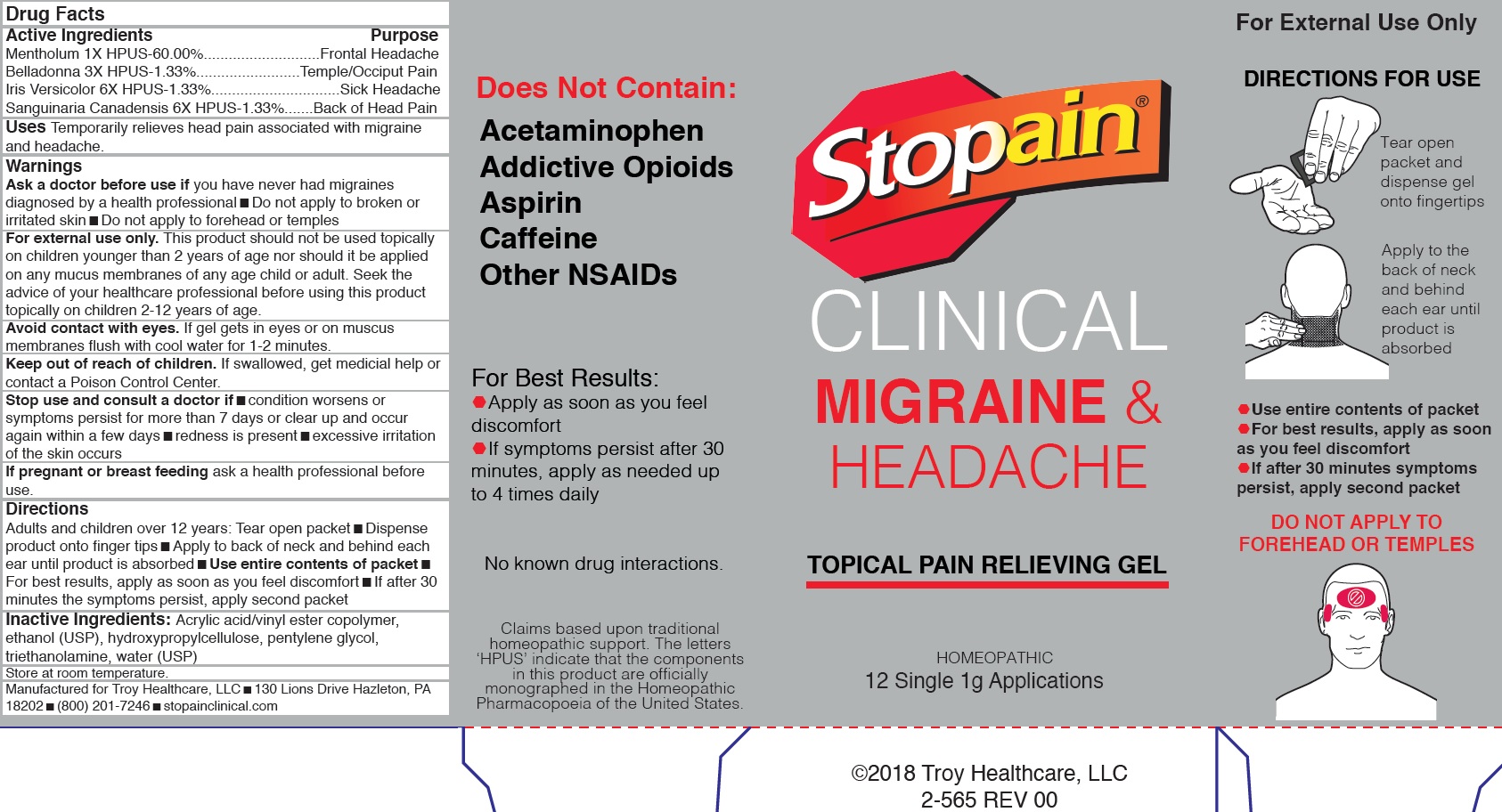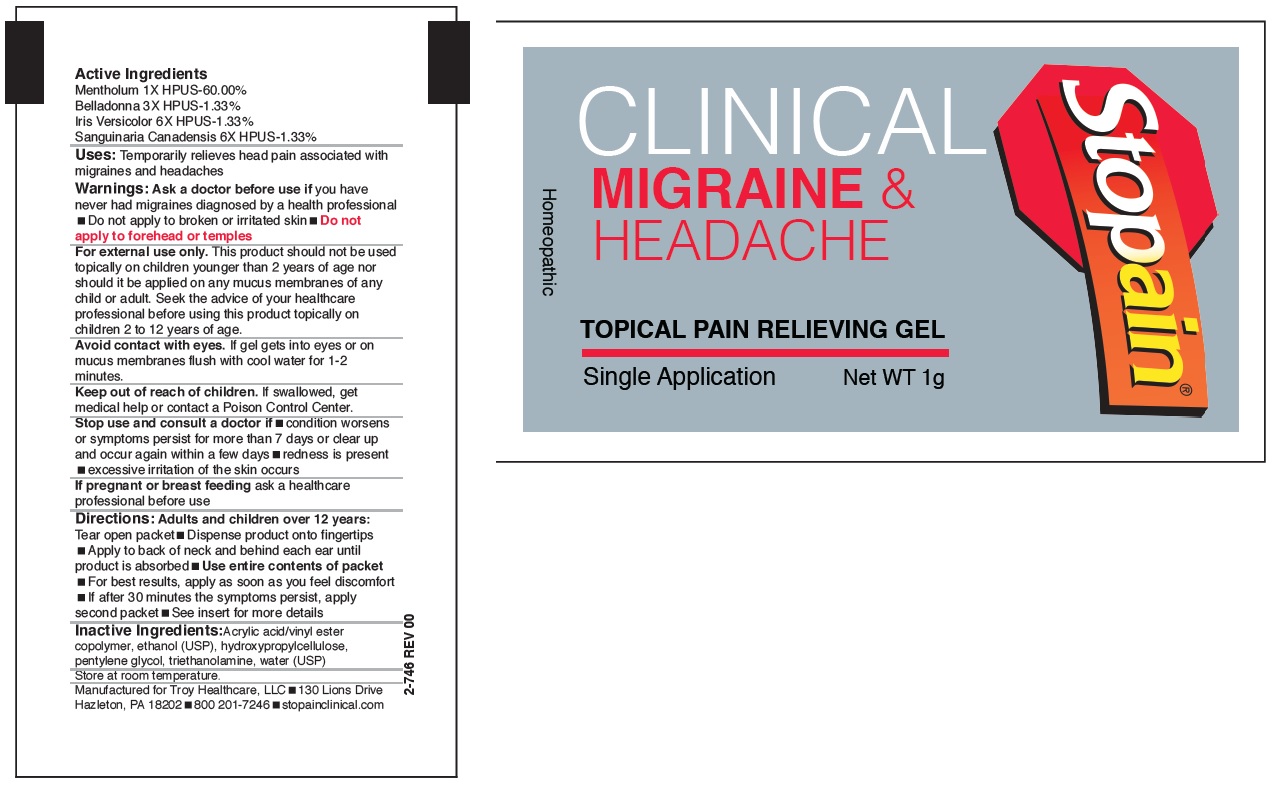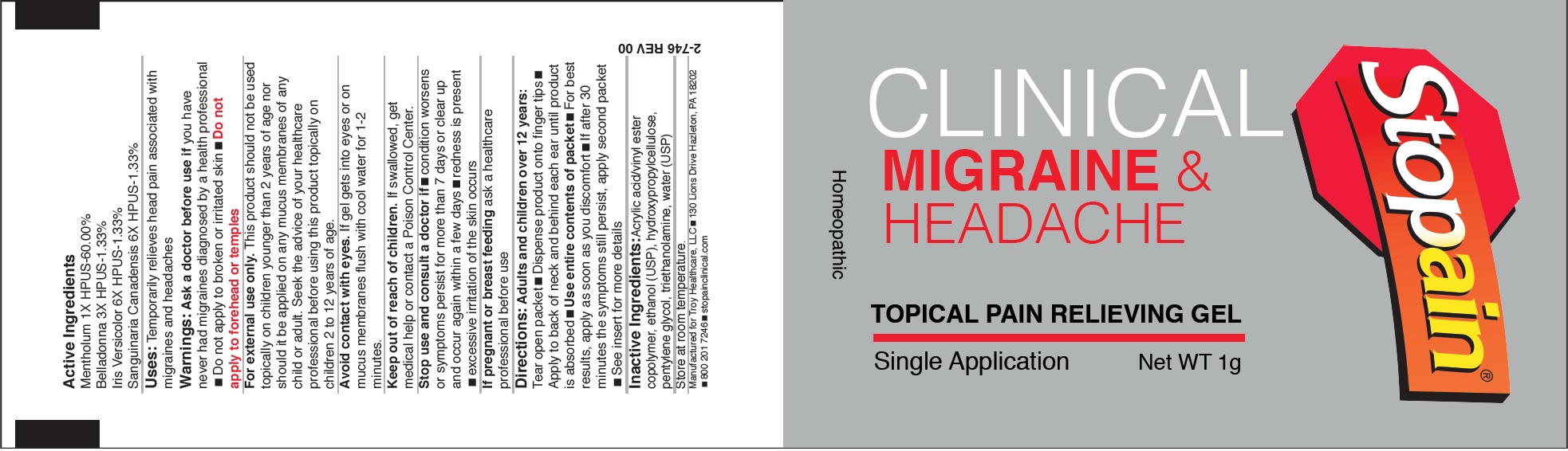 DRUG LABEL: STOPAIN CLINICAL Migraine and Headache
NDC: 63936-9700 | Form: GEL
Manufacturer: Troy Manufacturing, Inc.
Category: homeopathic | Type: HUMAN OTC DRUG LABEL
Date: 20230125

ACTIVE INGREDIENTS: MENTHOL, UNSPECIFIED FORM 1 [hp_X]/1 g; ATROPA BELLADONNA 3 [hp_X]/1 g; IRIS VERSICOLOR ROOT 6 [hp_X]/1 g; SANGUINARIA CANADENSIS ROOT 6 [hp_X]/1 g
INACTIVE INGREDIENTS: HYDROXYPROPYL CELLULOSE, UNSPECIFIED; PENTYLENE GLYCOL; TROLAMINE; WATER

STOPAIN CLINICAL Migraine & Headache

Active Ingredients

Mentholum 1X HPUS-60.00%

Belladonna 3X HPUS-1.33%

Iris Versicolor 6X HPUS-1.33%

Sanguinaria Canadensis 6X HPUS-1.33%

Purpose

Frontal Headache

Temple/Occiput Pain

Sick Headache

Back of Head Pain

Uses

Temporarily relieves head pain associated with migraine and headache.

Warnings

For external use only. This product should not be used topically on children younger than 2 years of age nor should it be applied on any mucus membranes of any age child or adult. Seek the advice of your healthcare professional before using this product topically on children 2-12 years of age.

Avoid contact with eyes. If gel gets in eyes or on muscus membranes flush with cool water for 1-2 minutes

Ask a doctor before use if

you have never had migraines diagnosed by a health professional

• Do not apply to broken or irritated skin

• Do not apply to forehead or temples

Keep out of reach of children.

If swallowed, get medicial help or contact a Poison Control Center.

Stop use and consult a doctor if

• condition worsens or symptoms persist for more than 7 days or clear up and occur again within a few days

• redness is present • excessive irritation of the skin occurs

If pregnant or breast feeding

ask a health professional before use.

Directions

• Adults and children over 12 years: Tear open packe • Dispense product onto finger tips • Apply to back of neck and behind each ear until product is absorbed • Use entire contents of packet • For best results, apply as soon as you feel discomfort • If after 30 minutes the symptoms persist, apply second packet

Inactive Ingredients:

Acrylic acid/vinyl ester copolymer, ethanol (USP), hydroxypropylcellulose, pentylene glycol, triethanolamine, water (USP)

Store at room temperature.

Manufactured for Troy Healthcare, LLC • 130 Lions Drive Hazleton, PA 18202 • (800) 201-7246 • stopainclinical.com